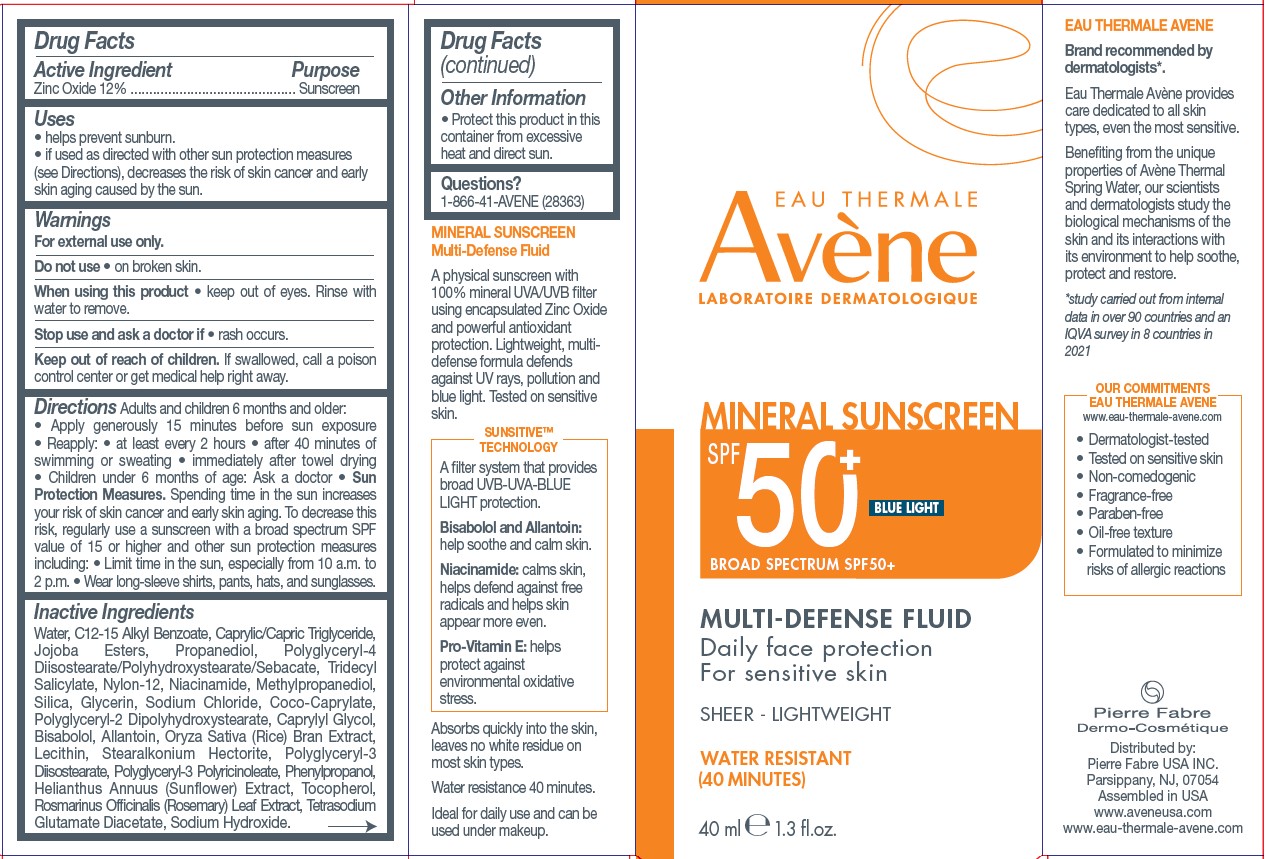 DRUG LABEL: Avene Multi-Defense Fluid
NDC: 64760-778 | Form: LOTION
Manufacturer: Pierre Fabre USA Inc.
Category: otc | Type: HUMAN OTC DRUG LABEL
Date: 20240308

ACTIVE INGREDIENTS: ZINC OXIDE 120 mg/1 mL
INACTIVE INGREDIENTS: MEDIUM-CHAIN TRIGLYCERIDES; PROPANEDIOL; CAPRYLYL GLYCOL; TOCOPHEROL; TETRASODIUM GLUTAMATE DIACETATE; TRIDECYL SALICYLATE; NYLON-12; NIACINAMIDE; METHYLPROPANEDIOL; SILICON DIOXIDE; ALLANTOIN; STEARALKONIUM HECTORITE; WATER; JOJOBA OIL, RANDOMIZED; POLYGLYCERYL-4 DIISOSTEARATE/POLYHYDROXYSTEARATE/SEBACATE; GLYCERIN; SODIUM CHLORIDE; POLYGLYCERYL-2 DIPOLYHYDROXYSTEARATE; LEVOMENOL; RICE BRAN; SOYBEAN LECITHIN; PHENYLPROPANOL; ROSEMARY; POLYGLYCERYL-3 DIISOSTEARATE; SODIUM HYDROXIDE; ALKYL (C12-15) BENZOATE; COCO-CAPRYLATE; POLYGLYCERYL-3 PENTARICINOLEATE; HELIANTHUS ANNUUS FLOWERING TOP

Avene Multi-Defense Fluid

Active ingredient

Zinc Oxide 12%

Purpose

Sunscreen

Uses

• helps prevent sunburn.

• if used as directed with other sun protection measures (see Directions), decreases the risk of skin cancer and early skin aging caused by the sun.

Warnings

For external use only.

Do not use

• on broken skin.

Stop use and ask a doctor if

• rash occurs.

Keep out of reach of children.

If swallowed, call a poison control center or get medical help right away.

Directions

Adults and children 6 months and older:

• Apply generously 15 minutes before sun exposure • Reapply: • at least every 2 hours • after 40 minutes of swimming or sweating • immediately after towel drying • Children under 6 months of age: Ask a doctor • Sun Protection Measures. Spending time in the sun increases your risk of skin cancer and early skin aging. To decrease this risk, regularly use a sunscreen with a broad spectrum SPF value of 15 or higher and other sun protection measures including: • Limit time in the sun, especially from 10 a.m. to 2 p.m. • Wear long-sleeve shirts, pants, hats, and sunglasses.

Inactive Ingredients

Water, C12-15 Alkyl Benzoate, Caprylic/Capric Triglyceride, Jojoba Esters, Propanediol, Polyglyceryl-4 Diisostearate/Polyhydroxystearate/Sebacate, Tridecyl Salicylate, Nylon-12, Niacinamide, Methylpropanediol, Silica, Glycerin, Sodium Chloride, Coco-Caprylate, Polyglyceryl-2 Dipolyhydroxystearate, Caprylyl Glycol, Bisabolol, Allantoin, Oryza Sativa (Rice) Bran Extract, Lecithin, Stearalkonium Hectorite, Polyglyceryl-3 Diisostearate, Polyglyceryl-3 Polyricinoleate, Phenylpropanol, Helianthus Annuus (Sun‑ower) Extract, Tocopherol, Rosmarinus Ofcinalis (Rosemary) Leaf Extract, Tetrasodium Glutamate Diacetate, Sodium Hydroxide.

Other Information

• Protect this product in this container from excessive heat and direct sun.

Questions?

1-866-41-AVENE (28363)